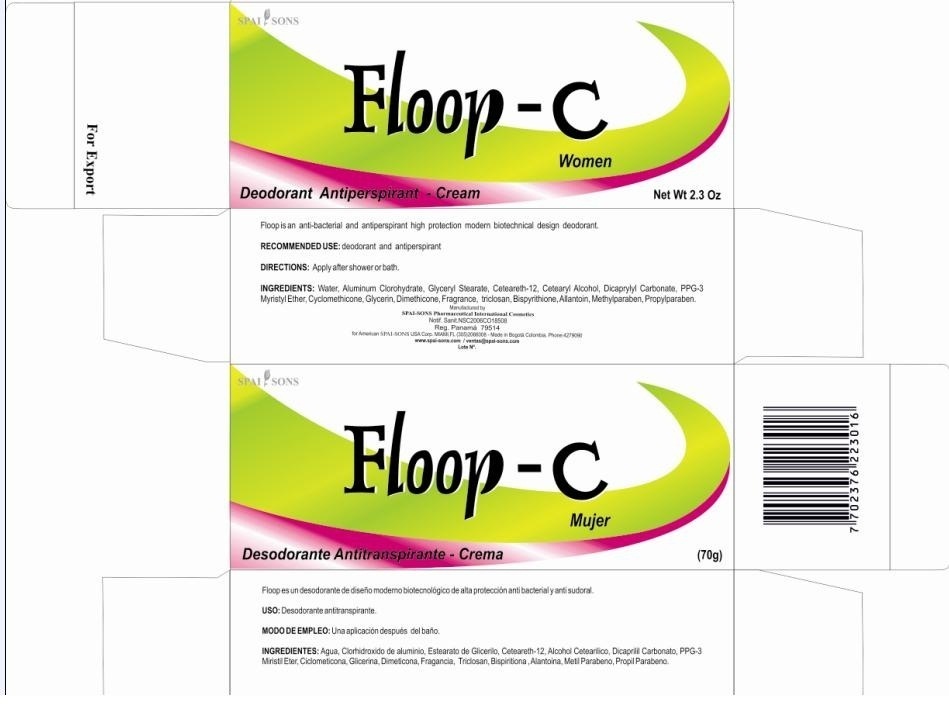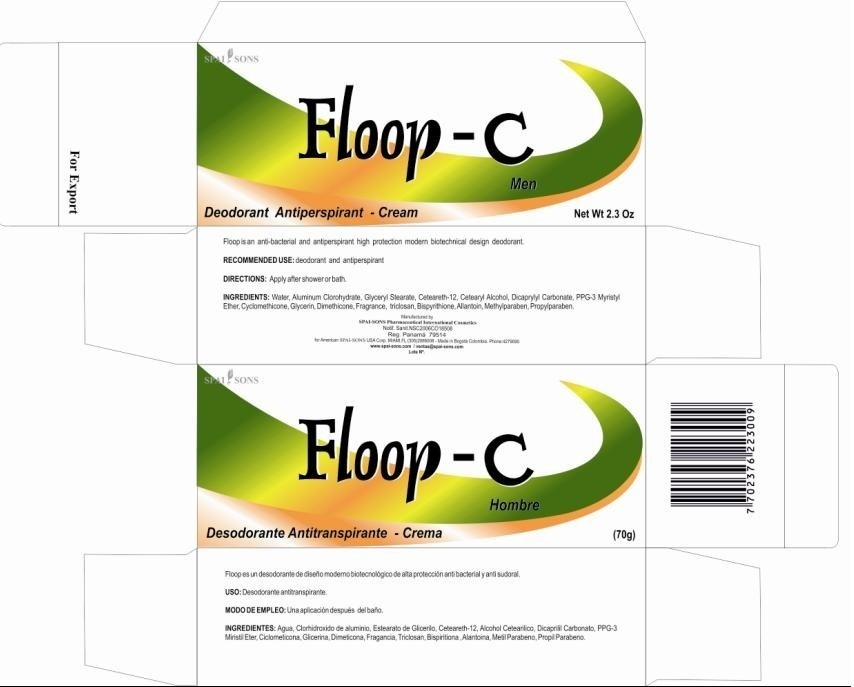 DRUG LABEL: SPAI-SONS
NDC: 66854-006 | Form: CREAM
Manufacturer: SPAI SONS PHARMACEUTICAL INTERNATIONAL COSMETICS
Category: otc | Type: HUMAN OTC DRUG LABEL
Date: 20120608

ACTIVE INGREDIENTS: ALUMINUM CHLOROHYDRATE 28 g/100 g
INACTIVE INGREDIENTS: WATER; GLYCERYL MONOSTEARATE; CETEARETH-12; CETOSTEARYL ALCOHOL; DICAPRYLYL CARBONATE; PPG-3 MYRISTYL ETHER; CYCLOMETHICONE; DIMETHICONE; GLYCERIN; DIPYRITHIONE; ALLANTOIN; METHYLPARABEN; PROPYLPARABEN; TRICLOSAN

SPAI-SONS FLOOP C

ACTIVE INGREDIENT

This product is owned as a deodorant active ingredients triclosan and aluminum chlorhydroxide. Mixed effect that produced is deodorant and antiperspirant.

PURPOSE

Floop is an anti-bacterial and antiperspirant high protection modern biotechnical design deodorant.

KEEP OUT OF REACH OF CHILDREN

This product must be keep out reach of the children.

INDICATIONS AND USAGE

This product is designed for use in armpit areas as may cause irritation in the area of application by the sensitivity of the user.

WARNINGS

Hypersensivity may result in the area of application, not consume this product, if swallowed consult your doctor.

DOSAGE AND ADMINISTRATION

This product is topical application apply the amount necessary in desirable area and rub gently.

INACTIVE INGREDIENT

The design of this product does humectant agents to give best feeling in the skin effect in adittion to produce antiperspirant and deodorant.

IMAGE OF THE CARTON LABEL